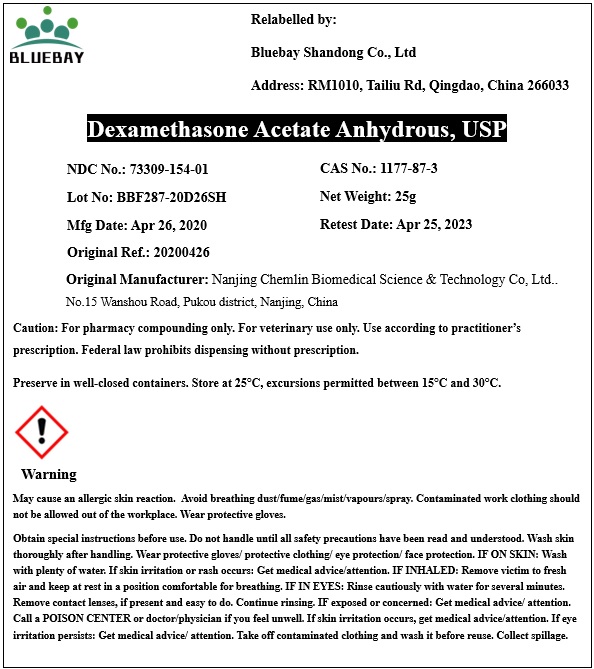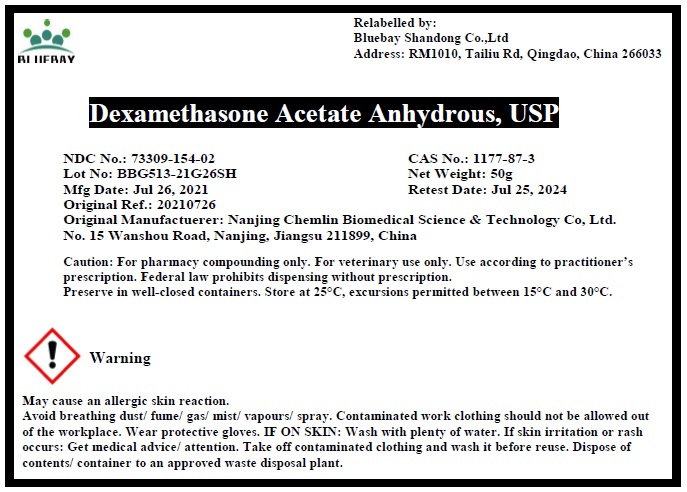 DRUG LABEL: Dexamethasone Acetate Anhydrous
NDC: 73309-154 | Form: POWDER
Manufacturer: BLUEBAY SHANDONG CO.,LTD
Category: other | Type: BULK INGREDIENT
Date: 20211007

ACTIVE INGREDIENTS: DEXAMETHASONE ACETATE ANHYDROUS 1 g/1 g

Dexamethasone Acetate Anhydrous